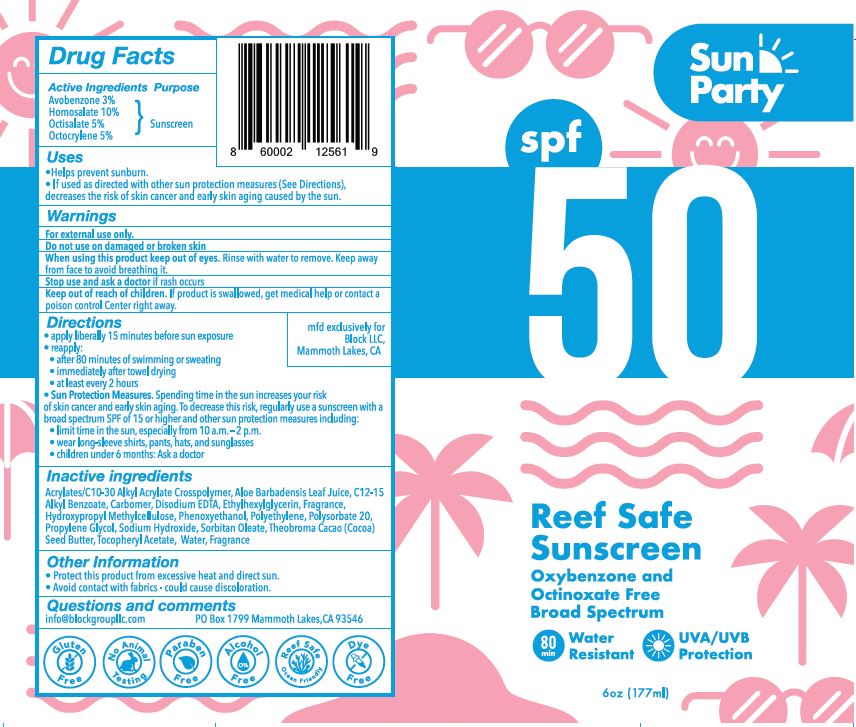 DRUG LABEL: SUN PARTY SUNSCREEN
NDC: 76853-108 | Form: LOTION
Manufacturer: Block LLC
Category: otc | Type: HUMAN OTC DRUG LABEL
Date: 20200823

ACTIVE INGREDIENTS: AVOBENZONE 3 g/100 mL; HOMOSALATE 10 g/100 mL; OCTISALATE 5 g/100 mL; OCTOCRYLENE 5 g/100 mL
INACTIVE INGREDIENTS: CARBOMER INTERPOLYMER TYPE A (ALLYL SUCROSE CROSSLINKED); ALOE VERA LEAF; ALKYL (C12-15) BENZOATE; CARBOMER HOMOPOLYMER, UNSPECIFIED TYPE; EDETATE DISODIUM; ETHYLHEXYLGLYCERIN; HYPROMELLOSE, UNSPECIFIED; PHENOXYETHANOL; HIGH DENSITY POLYETHYLENE; POLYSORBATE 20; PROPYLENE GLYCOL; SODIUM HYDROXIDE; SORBITAN MONOOLEATE; COCOA BUTTER; .ALPHA.-TOCOPHEROL ACETATE; WATER

SUN PARTY SUNSCREEN SPF 50

ACTIVE INGREDIENTS

AVOBENZONE 3%

HOMOSALATE 10%

OCTISALATE 5%

OCTOCRYLENE 5%

PURPOSE

SUNSCREEN

USES

- HELPS PREVENT SUNBURN.
- IF USED AS DIRECTED WITH OTHER SUN PROTECTION MEASURES (SEE DIRECTIONS), DECREASES THE RISK OF SKIN CANCER, EARLY SKIN AGING BY THE SUN.

WARNING

FOR EXTERNAL USE ONLY.

DO NOT USE ON DAMAGED OR BROKEN SKIN.

WHEN USING THIS PRODUCT KEEP OUT OF EYES. RINSE WITH WATER TO REMOVE. KEEP AWAY FROM FACE TO AVOID BREATHING IT.

STOP USE AND CONTACT A DOCTOR IS RASH OCCURS.

KEEP OUT OF REACH OF CHILDREN. IF PRODUCT IS SWALLOWED, GET MEDICAL HELP OR CONTACT A POISON CONTROL CENTER RIGHT AWAY.

DIRECTIONS

APPLY LIBERALLY 15 MINUTES BEFORE SUN EXPOSURE.

REAPPLY:

- AFTER 80 MINUTES OF SWIMMING OR SWEATING
- IMMEDIATELY AFTER TOWEL DRYING
- AT LEAST EVERY 2 HOURS

SUN PROTECTION MEASURES. SPENDING TIME IN THE SUN INCREASES YOUR RISK OF SKIN CANCER AND EARLY SKIN AGING. TO DECREASE THE RISK, REGULARLY USE A SUNSCREEN WITH A BROAD SPECTRUM SPF OF 15 OR HIGHER AND OTHER SUN PROTECTION MEASURES INCLUDING:

- LIMIT TIME IN THE SUN, ESPECIALLY FROM 10 A.M. - 2 P.M.
- WEAR LONG-SLEEVE SHIRTS, PANTS, HATS AND SUNGLASSES
- CHILDREN UNDER 6 MONTHS: ASK A DOCTOR

INACTIVE INGREDIENTS

Acrylates/C10-30 Alkyl Acrylate Crosspolymer, Aloe Barbadensis Leaf Juice, C12-15 Alkyl Benzoate, Carbomer, Disodium EDTA, Ethylhexylglycerin, Fragrance, Hydroxypropyl Methylcellulose, Phenoxyethanol, Polyethylene, Polysorbate 20, Propylene Glycol, Sodium Hydroxide, Sorbitan Oleate, Theobroma Cacao (Cocoa) Seed Butter, Tocopheryl Acetate, Water, Fragrance

OTHER INFORMATION

- PROTECT THIS PRODUCT FROM EXCESSIVE HEAT AND DIRECT SUN.
- AVOID CONTACT WITH FABRICS - COULD CAUSE DISCOLORATION.

QUESTIONS AND COMMENTS

INFO@BLOCKLLC.COM

PO BOX 1799 MAMMOTH LAKES, CA 93546